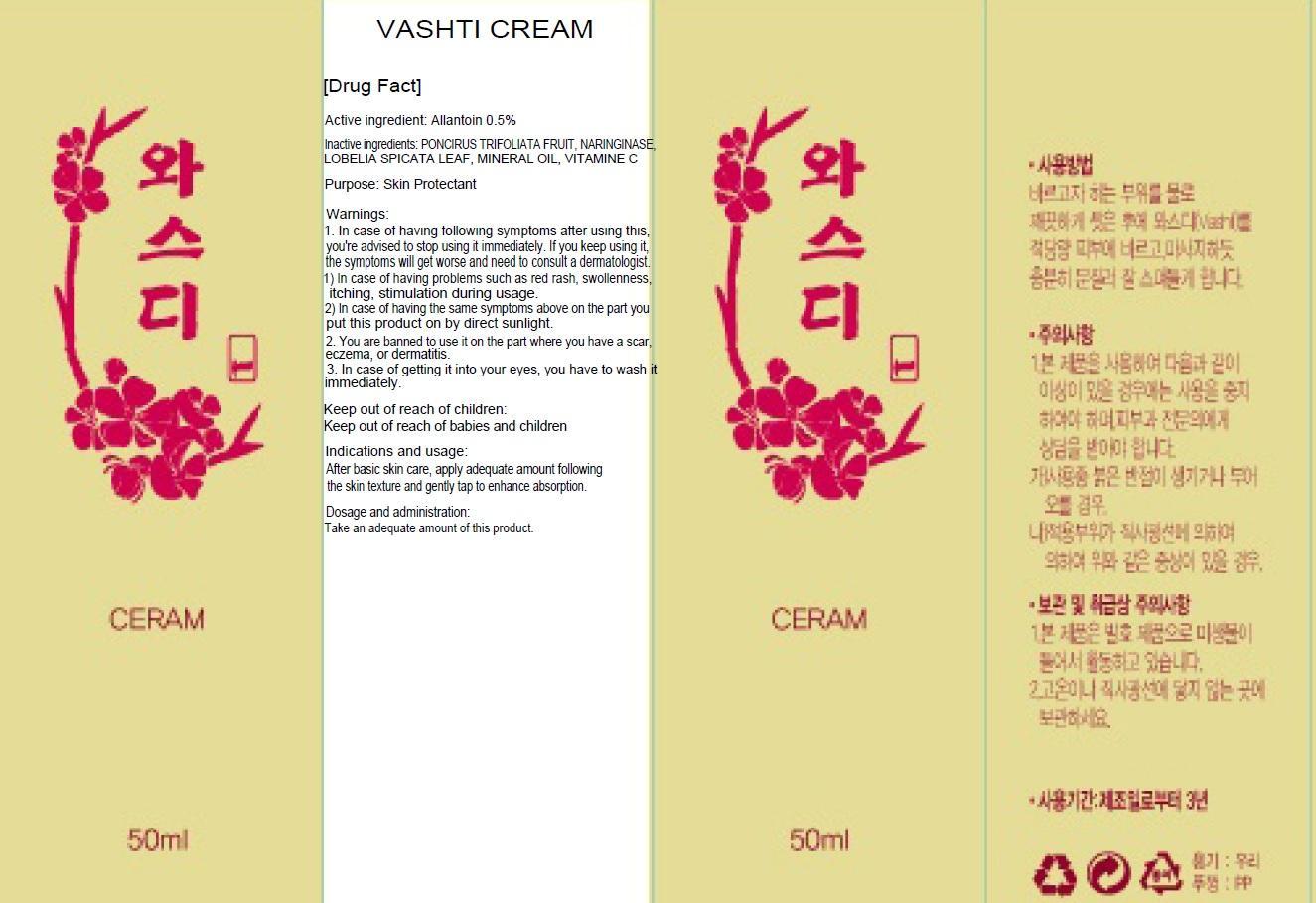 DRUG LABEL: VASHTI
NDC: 61221-020 | Form: CREAM
Manufacturer: LEADER GREEN CO., LTD.
Category: otc | Type: HUMAN OTC DRUG LABEL
Date: 20130830

ACTIVE INGREDIENTS: Allantoin 0.25 mg/50 mL
INACTIVE INGREDIENTS: LOBELIA SPICATA LEAF

ACTIVE INGREDIENT

Active ingredient: Allantoin 0.5%

INACTIVE INGREDIENT

Inactive ingredients: PONCIRUS TRIFOLIATA FRUIT, NARINGINASE, LOBELIA SPICATA LEAF, MINERAL OIL, VITAMINE C

Purpose

Purpose: Skin Protectant

WARNINGS

1. In case of having following symptoms after using this, you're advised to stop using it immediately. If you keep using it, the symptoms will get worse and need to consult a dermatologist.
1) In case of having problems such as red rash, swollenness, itching, stimulation during usage.
2) In case of having the same symptoms above on the part you put this product on by direct sunlight.
2. You are banned to use it on the part where you have a scar, eczema, or dermatitis.
3. In case of getting it into your eyes, you have to wash it immediately.

KEEP OUT OF REACH OF CHILDREN

Keep out of reach of babies and children

Indications and usage

After basic skin care, apply adequate amount following the skin texture and gently tap to enhance absorption.

Dosage and administration

Take an adequate amount of this product.